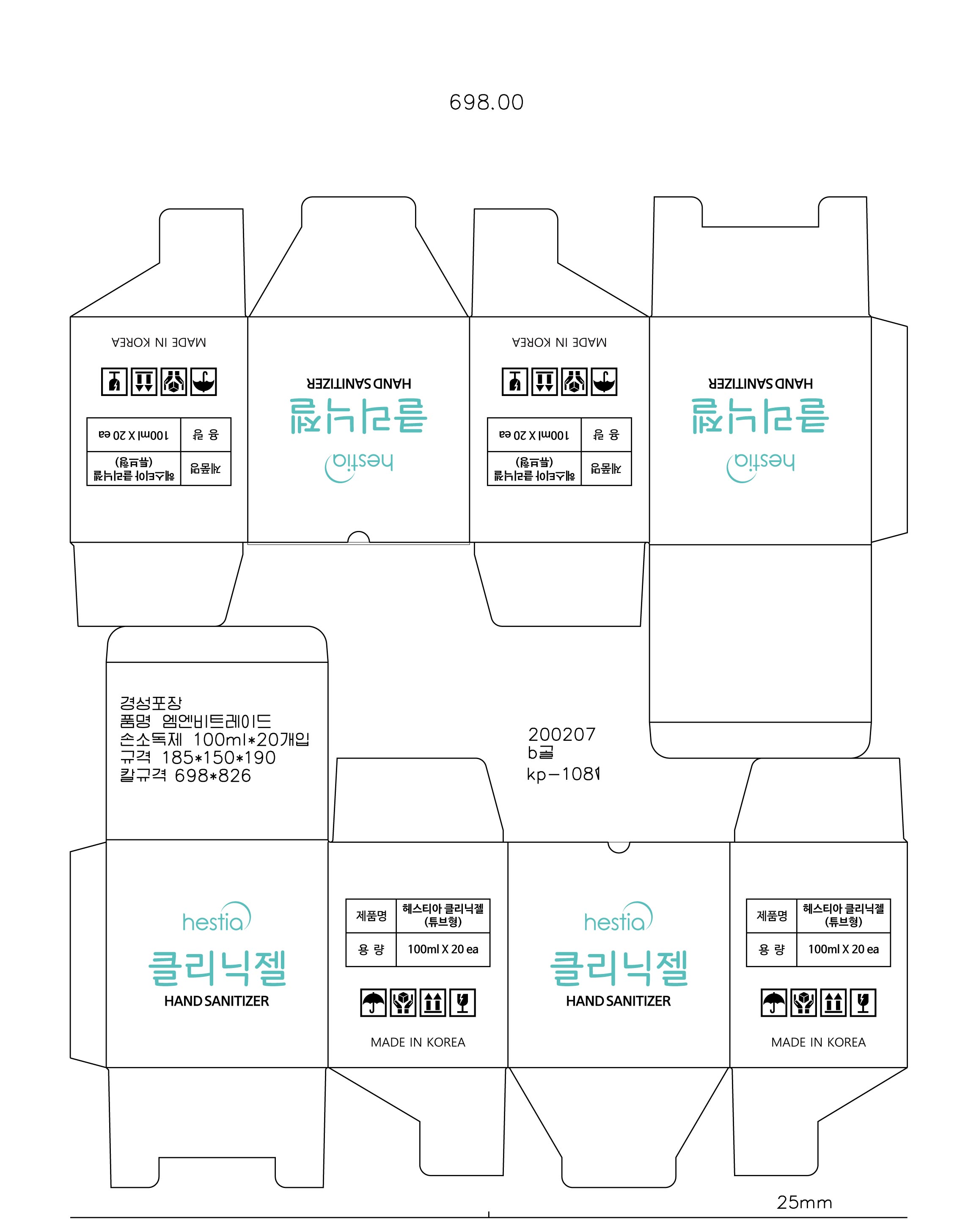 DRUG LABEL: Hestia Clinic Gel Hand Sanitizer
NDC: 74002-0100 | Form: GEL
Manufacturer: DongbangCosmetics Co., ltd.
Category: otc | Type: HUMAN OTC DRUG LABEL
Date: 20200413

ACTIVE INGREDIENTS: ALCOHOL 62 g/100 mL
INACTIVE INGREDIENTS: BUTYLENE GLYCOL; WATER

Drug Facts

ACTIVE INGREDIENT

Alcohol

INACTIVE INGREDIENT

Water, Carbomer, Triethanolamine, Butylene Glycol, etc.

PURPOSE

Antiseptic

KEEP OUT OF REACH OF THE CHILDREN

INDICATIONS AND USAGE

Store under 30°C (86°F)

WARNINGS

For external use only.

Flammable, keep away from fire or flame.

When using this product keep out of eyes. If contact with eyes occurs, rinse promptly and thoroughly with water.

Stop use and ask a doctor if significant irritation or sensitization develops.

Keep out of reach of children. If swallowed, get medical help or contact a Poison Control Center right away.

DOSAGE AND ADMINISTRATION

Take an appropriate amount of hand sanitizing gel on your hand.

Rub your palms.

Clasp and rub it between your fingers.

Once again, take an appropriate amount of the gel on your hand.

Rub the fingernails of both hands.

Cover your finger with your palm and rub it.